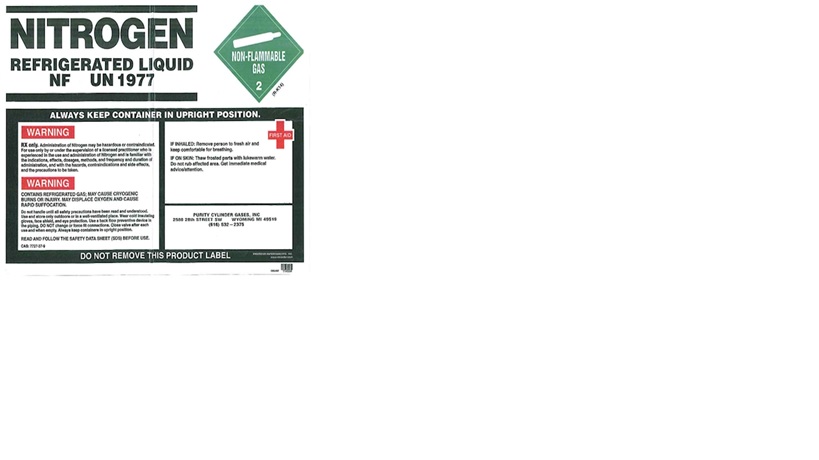 DRUG LABEL: NITROGEN
NDC: 10927-106 | Form: LIQUID
Manufacturer: PURITY CYLINDER GASES INC
Category: prescription | Type: HUMAN PRESCRIPTION DRUG LABEL
Date: 20181031

ACTIVE INGREDIENTS: NITROGEN 99 L/100 L

PACKAGE LABEL

NITROGEN REFRIGERATED LIQUID NF
UN 1977
ALWAYS KEEP CONTAINER IN UPRIGHT POSITION.
WARNING
RX only. Administration of Nitrogen may be hazardous or contraindicated. For use only by or under the supervision of a licensed practitioner who is experienced in the use and administration of Nitrogen and is familiar with indications, effects, dosages, methods, and frequency and duration of administration, and with the hazards, contraindications and side effects, and the precautions to be taken.
WARNING
CONTAINS REFRIGERATED GAS; MAY CAUSE CRYOGENIC BURNS OR INJURY. MAY DISPLACE OXYGEN AND CAUSE RAPID SUFFOCATION.
Do not handle until all safety precautions have been read and understood. Use and store only outdoors or in a well-ventilated place. Wear cold insulating gloves, face shield, and eye protection. Use a back flow preventive device in the piping. DO NOT change or force fit connections. Close valve after each use and when empty. Always keep containers in upright position.
READ AND FOLLOW THE SAFETY DATA SHEET (SDS) BEFORE USE.
CAS: 77227-37-9
FIRST AID
IF INHALED: Remove person to fresh air and keep comfortable for breathing.
IF ON SKIN: Thaw frosted parts with lukewarm water. Do not rub affected area. Get immediate medical advice/attention.
PURITY CYLINDER GASES, INC.
2580 28TH ST SW, WYOMING, MI 49519
616-532-2375
DO NOT REMOVE THIS PRODUCT LABEL